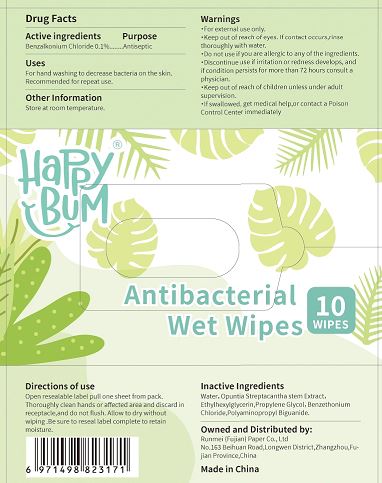 DRUG LABEL: Antibacterial Wet Wipes
NDC: 81472-101 | Form: SOLUTION
Manufacturer: Runmei Paper (Fujian) Co., Ltd.
Category: otc | Type: HUMAN OTC DRUG LABEL
Date: 20210416

ACTIVE INGREDIENTS: BENZALKONIUM CHLORIDE 0.01 g/1 1
INACTIVE INGREDIENTS: POLYAMINOPROPYL BIGUANIDE; PROPYLENE GLYCOL; WATER; ETHYLHEXYLGLYCERIN; OPUNTIA STREPTACANTHA STEM

Runmei - Happy Bum Antibacterial Wet Wipes

ACTIVE INGREDIENT

BENZALKONIUM CHLORIDE 0.1%

PURPOSE

ANTISEPTIC

USES

FOR HAND WASHING TO DECREASE BACTERIA ON THE SKIN. RECOMMENDED FOR REPEAT USE.

Warning

- For external use only
- Keep out of reach of eyes. If contact occurs, rinse throughtly with water.
- Do not use if you are allergic to any of the ingredients.
- Discontinue use if irritation or redness develops, and if condition persists for more than 72 hours consult a physician.
- Keep out of reach of children unless under adult supervision.
- If swollowed, get medical help, or contact a Poison Control Center immediately.

KEEP OUT OF REACH OF CHILDREN UNLESS UNDER ADULT SUPERVISION.

IF SWALLOWED, GET MEDICAL HELP OR CONTACT A POISON CONTROL CENTER IMMEDIATELY.

Directions of Use

Open resealabel label pull one sheetfrom pack. Thoroughly clean hands or affected area and discard in receptacle, and do not flush. Allow to dry without wiping. Be sure to reseal label complete to retain moisture.

INACTIVE INGREDIENTS

Water, Opuntia Streptacantha stem Extract, Ethylhexylglycerin, Propylene Glycol, Benzethonium Chloride, Polyaminopropyl Biguanide